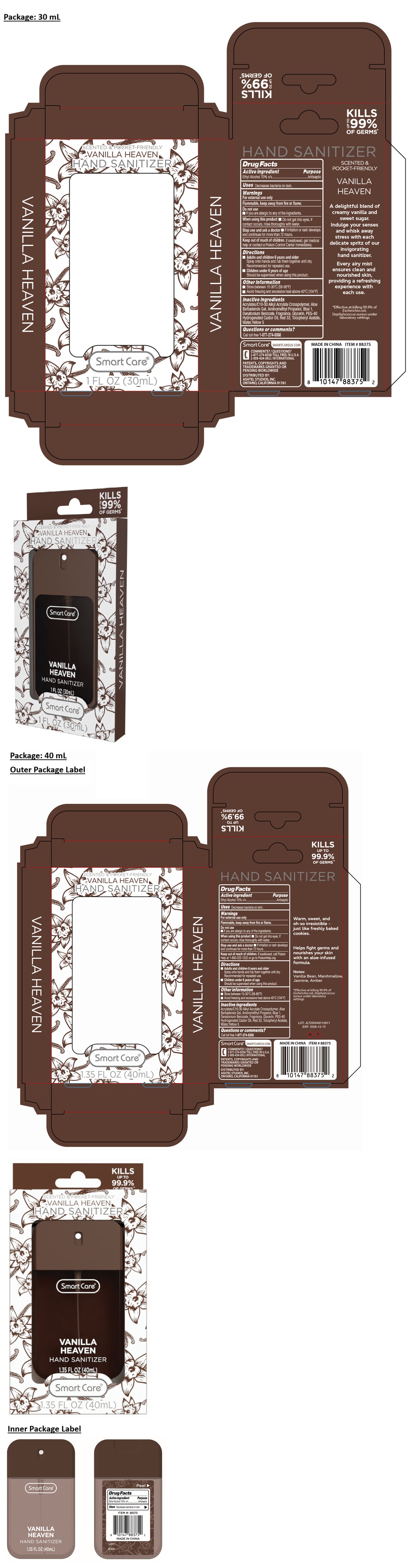 DRUG LABEL: Smart Care VANILLA HEAVEN HAND SANITIZER
NDC: 70108-135 | Form: SPRAY
Manufacturer: Ashtel Studios, Inc.
Category: otc | Type: HUMAN OTC DRUG LABEL
Date: 20260217

ACTIVE INGREDIENTS: ALCOHOL 70 mL/100 mL
INACTIVE INGREDIENTS: ACRYLATES/C10-30 ALKYL ACRYLATE CROSSPOLYMER (60000 MPA.S); ALOE VERA LEAF; AMINOMETHYLPROPANOL; FD&C BLUE NO. 1; DENATONIUM BENZOATE; GLYCERIN; POLYOXYL 40 HYDROGENATED CASTOR OIL; D&C RED NO. 33; .ALPHA.-TOCOPHEROL ACETATE; WATER; FD&C YELLOW NO. 5

Smart Care® VANILLA HEAVEN HAND SANITIZER

Active ingredient

Ethyl Alcohol 70% v/v

Purpose

Antiseptic

Uses

Decreases bacteria on skin.

Warnings

For external use only

Flammable, keep away from fire or flame.

Do not use
• If you are allergic to any of the ingredients.

When using this product • Do not get into eyes. If contact occurs, rinse thoroughly with water.

Stop use and ask a doctor • If irritation or rash develops and continues for more than 72 hours.

Keep out of reach of children. If swallowed, call Poison Help at 1-800-222-1222 or go to PoisonHelp.org.

Directions

• Adults and children 6 years and older
Spray onto hands and rub them together until dry. Recommended for repeated use.

• Children under 6 years of age
Should be supervised when using this product.

Other information

• Store between 15-30°C (59-86°F)
• Avoid freezing and excessive heat above 40°C (104°F)

Inactive ingredients

Acrylates/C10-30 Alkyl Acrylate Crosspolymer, Aloe Barbadensis Gel, Aminomethyl Propanol, Blue 1, Denatonium Benzoate, Fragrance, Glycerin, PEG-40 Hydrogenated Castor Oil, Red 33, Tocopheryl Acetate, Water, Yellow 5

Questions or comments?

Call toll free 1-877-274-8358

SCENTED & POCKET-FRIENDLY

KILLS UP TO 99.9% OF GERMS*

A delightful blend of creamy vanilla and sweet sugar. Indulge your senses and whisk away stress with each delicate spritz of our invigorating hand sanitizer.

Every airy mist ensures clean and nourished skin, providing a refreshing experience with each use.

Warm, sweet, and oh-so irresistible - just like freshly baked cookies.

Helps fight germs and nourishes your skin with an aloe-infused formula.

Notes: Vanilla Bean, Marshmallow, Jasmine, Amber

*Effective at killing 99.9% of Escherichia coli, Staphylococcus aureus under laboratory settings

SmartCare® SMARTCAREUS.COM
1-909-434-0911 INTERNATIONAL

PATENTS, COPYRIGHTS AND TRADEMARKS GRANTED OR PENDING WORLDWIDE

DISTRIBUTED BY:
ASHTEL STUDIOS, INC.
ONTARIO, CALIFORNIA 91761

MADE IN CHINA